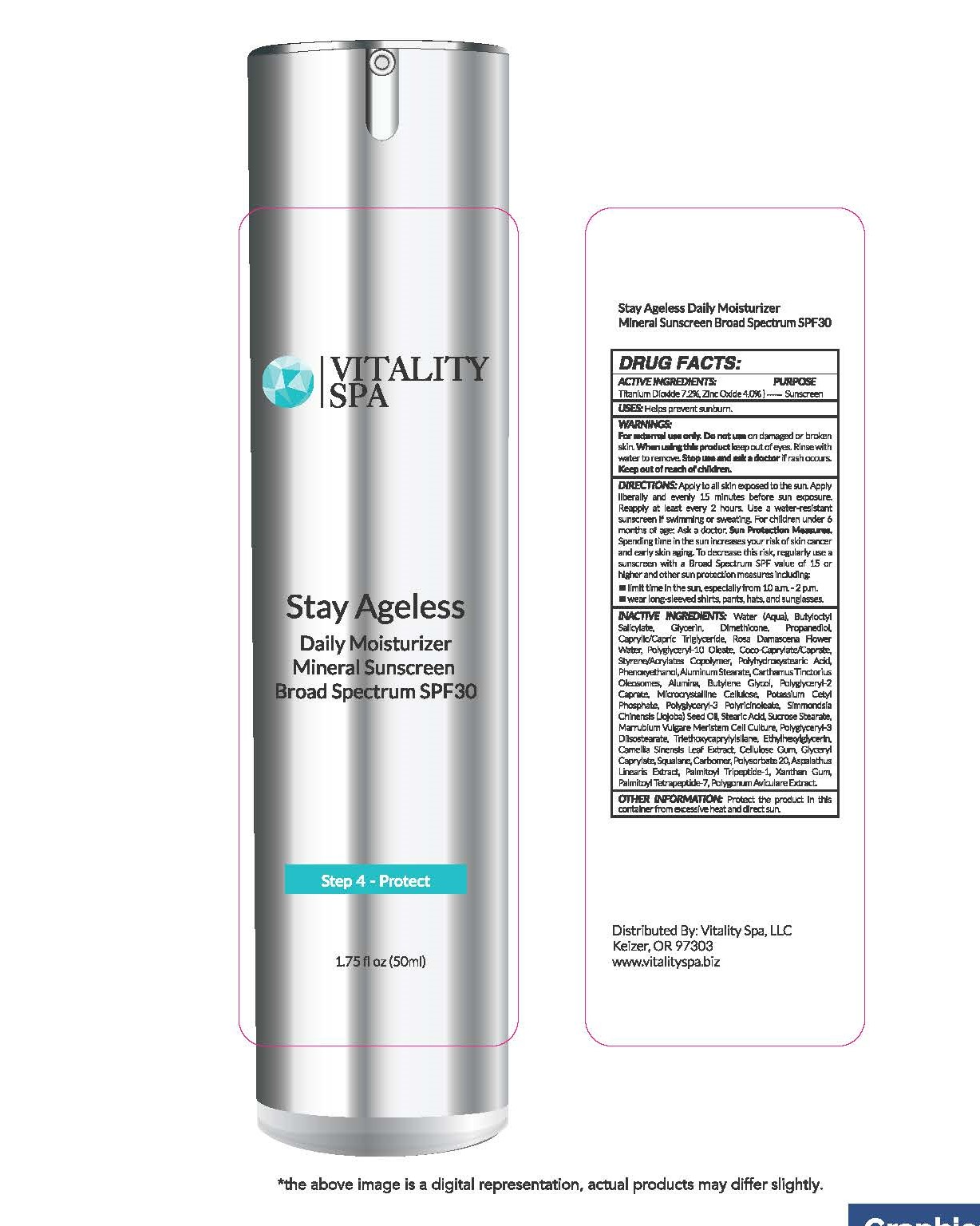 DRUG LABEL: Stay Ageless Daily Moisturizer Mineral Sunscreen Broad Spectrum SPF 30
NDC: 82633-2750 | Form: LIQUID
Manufacturer: Vitality Spa, LLC
Category: otc | Type: HUMAN OTC DRUG LABEL
Date: 20220322

ACTIVE INGREDIENTS: TITANIUM DIOXIDE 7.2 g/100 mL; ZINC OXIDE 4 g/100 mL
INACTIVE INGREDIENTS: ROSA X DAMASCENA FLOWER OIL; PHENOXYETHANOL; ALUMINUM STEARATE; CARTHAMUS TINCTORIUS SEED OLEOSOMES; ALUMINUM OXIDE; BUTYLENE GLYCOL; POLYGLYCERYL-2 CAPRATE; MICROCRYSTALLINE CELLULOSE; POTASSIUM CETYL PHOSPHATE; POLYGLYCERYL-3 PENTARICINOLEATE; JOJOBA OIL; STEARIC ACID; SUCROSE STEARATE; WATER; BUTYLOCTYL SALICYLATE; GLYCERIN; DIMETHICONE; MEDIUM-CHAIN TRIGLYCERIDES; PROPANEDIOL; POLYGLYCERYL-10 OLEATE; POLYGLYCERYL-3 DIISOSTEARATE; TRIETHOXYCAPRYLYLSILANE; ETHYLHEXYLGLYCERIN; GREEN TEA LEAF; CARBOXYMETHYLCELLULOSE SODIUM, UNSPECIFIED; GLYCERYL MONOCAPRYLATE; SQUALANE; CARBOMER HOMOPOLYMER, UNSPECIFIED TYPE; POLYSORBATE 20; PALMITOYL TRIPEPTIDE-1; XANTHAN GUM; PALMITOYL TETRAPEPTIDE-7; POLYGONUM AVICULARE TOP; COCOYL CAPRYLOCAPRATE

Stay Ageless Daily Moisturizer Mineral Sunscreen Broad Spectrum SPF 30 Sunscreen

DRUG FACTS:

ACTIVE INGREDIENTS

Titanium Dioxide 7.2%, Zinc Oxide 4.0%.

Purpose

Sunscreen

USES

Helps prevent sunburn.

WARNINGS

For external use only. Do not use on damaged or broken skin. When using this product keep out of eyes. Rinse with water to remove. Stop use and ask a doctor if rash occurs.

DIRECTIONS

Apply to all skin exposed to the sun. *Apply liberally and evenly 15 minutes before sun exposure. *Reapply at least every 2 hours. *Use a water-resistant sunscreen if swimming or sweating. *For children under 6 months of age: Ask a doctor. Sun Protection Measures. Spending time in the sun increases your risk of skin cancer and early skin aging. To decrease this risk, regularly use a sunscreen with a Broad Spectrum SPF value of 15 or higher and other sun protection measures including:

- limit time in the sun, especially from 10 a.m. - 2 p.m.
- wear long-sleeved shirts, pants, hats, and sunglasses.

INACTIVE INGREDIENTS

Water (Aqua), Butyloctyl Salicylate, Glycerin, Dimethicone, Caprylic/Capric Triglyceride, Propanediol, Polyglyceryl-10 Oleate, Coco-Caprylate/Caprate, Styrene/Acrylates Copolymer, Polyhydroxystearic Acid, Rosa Damascena Flower Water, Phenoxyethanol, Aluminum Stearate, Carthamus Tinctorius Oleosomes, Alumina, Butylene Glycol, Polyglyceryl-2 Caprate, Microcrystalline Cellulose, Potassium Cetyl Phosphate, Polyglyceryl-3 Polyricinoleate, Simmondsia Chinensis (Jojoba) Seed Oil, Stearic Acid, Sucrose Stearate, Marrubium Vulgare Meristem Cell Culture, Polyglyceryl-3 Diisostearate, Triethoxycaprylylsilane, Ethylhexylglycerin, Camellia Sinensis Leaf Extract, Cellulose Gum, Glyceryl Caprylate, Squalane, Carbomer, Polysorbate 20, Aspalathus Linearis Extract, Palmitoyl Tripeptide-1, Xanthan Gum, Palmitoyl Tetrapeptide-7, Polygonum Aviculare Extract.

OTHER INFORMATION

Protect the product in this container from excessive heat and direct sun.